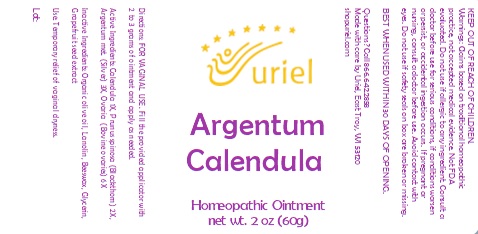 DRUG LABEL: Argentum Calendula
NDC: 48951-1364 | Form: OINTMENT
Manufacturer: Uriel Pharmacy Inc.
Category: homeopathic | Type: HUMAN OTC DRUG LABEL
Date: 20230922

ACTIVE INGREDIENTS: CALENDULA OFFICINALIS FLOWERING TOP 1 [hp_X]/1 g; SLOE 2 [hp_X]/1 g; SILVER 3 [hp_X]/1 g; BOS TAURUS OVARY 6 [hp_X]/1 g
INACTIVE INGREDIENTS: OLIVE OIL; LANOLIN; YELLOW WAX; GLYCERIN; CITRUS PARADISI SEED

Argentum Calendula

INDICATIONS AND USAGE

Directions: FOR VAGINAL USE.

DOSAGE AND ADMINISTRATION

Fill the provided applicator with 2 to 3 grams of ointment and apply as needed.

ACTIVE INGREDIENT

Active Ingredients: Calendula 1X, Prunus spinosa (Blackthorn) 2X, Argentum met. (Silver) 3X, Ovaria (Bovine ovaries) 6X

INACTIVE INGREDIENT

Inactive Ingredients: Organic olive oil, Lanolin, Beeswax, Glycerin, Grapefruit seed extract

PURPOSE

Use: Temporary relief of vaginal dryness.

KEEP OUT OF REACH OF CHILDREN.

WARNINGS

Warnings: Do not use if allergic to any ingredient. Consult a doctor before use for serious conditions, if conditions worsen or persist, or accidental ingestion occurs. If pregnant or nursing, consult a doctor before use. Avoid contact with eyes. Do not use if safety seals on box are broken or missing.

BEST WHEN USED WITHIN 30 DAYS OF OPENING.

QUESTIONS

Questions? Call 866.642.2858 Made with care by Uriel, East Troy, WI 53120 shopuriel.com Lot: